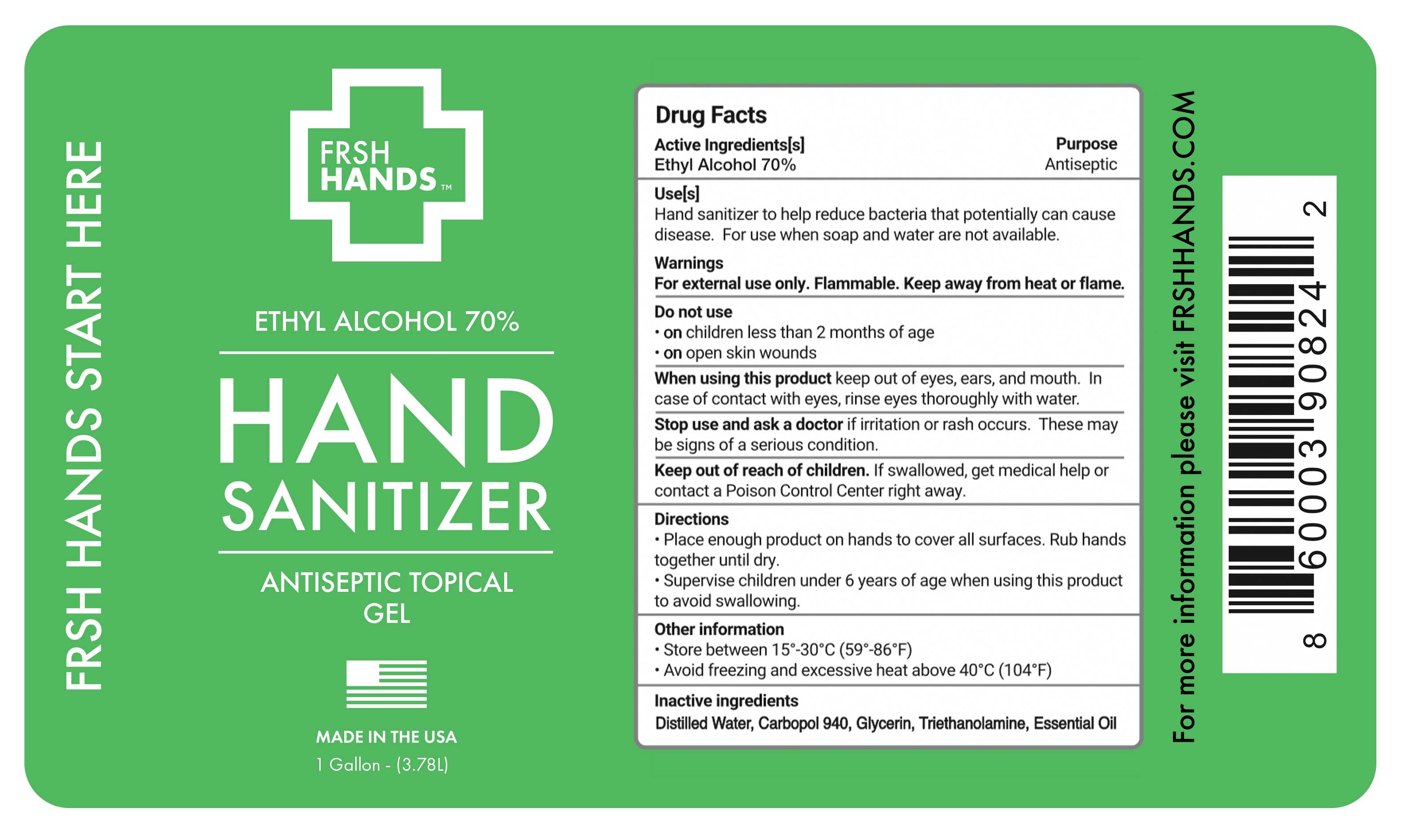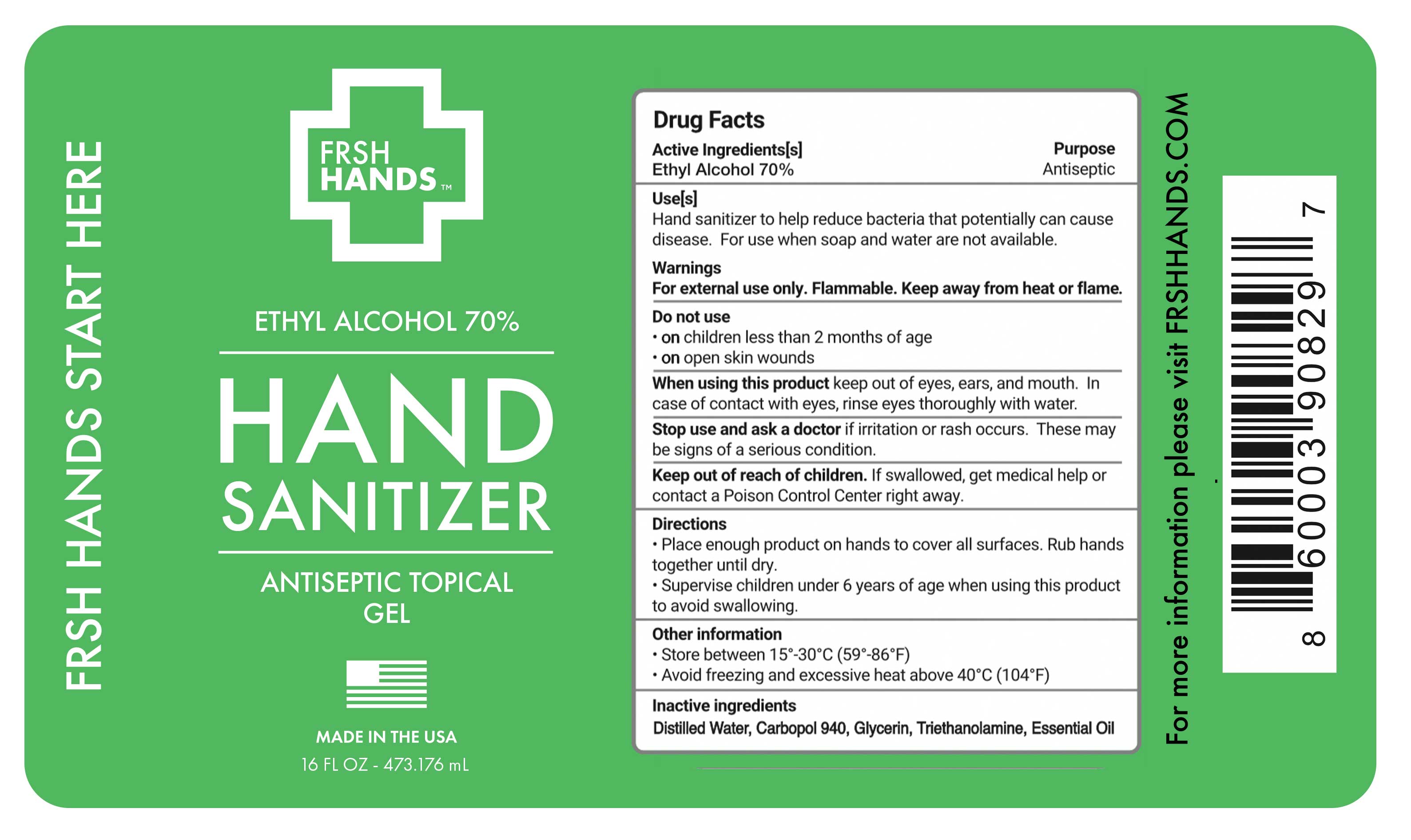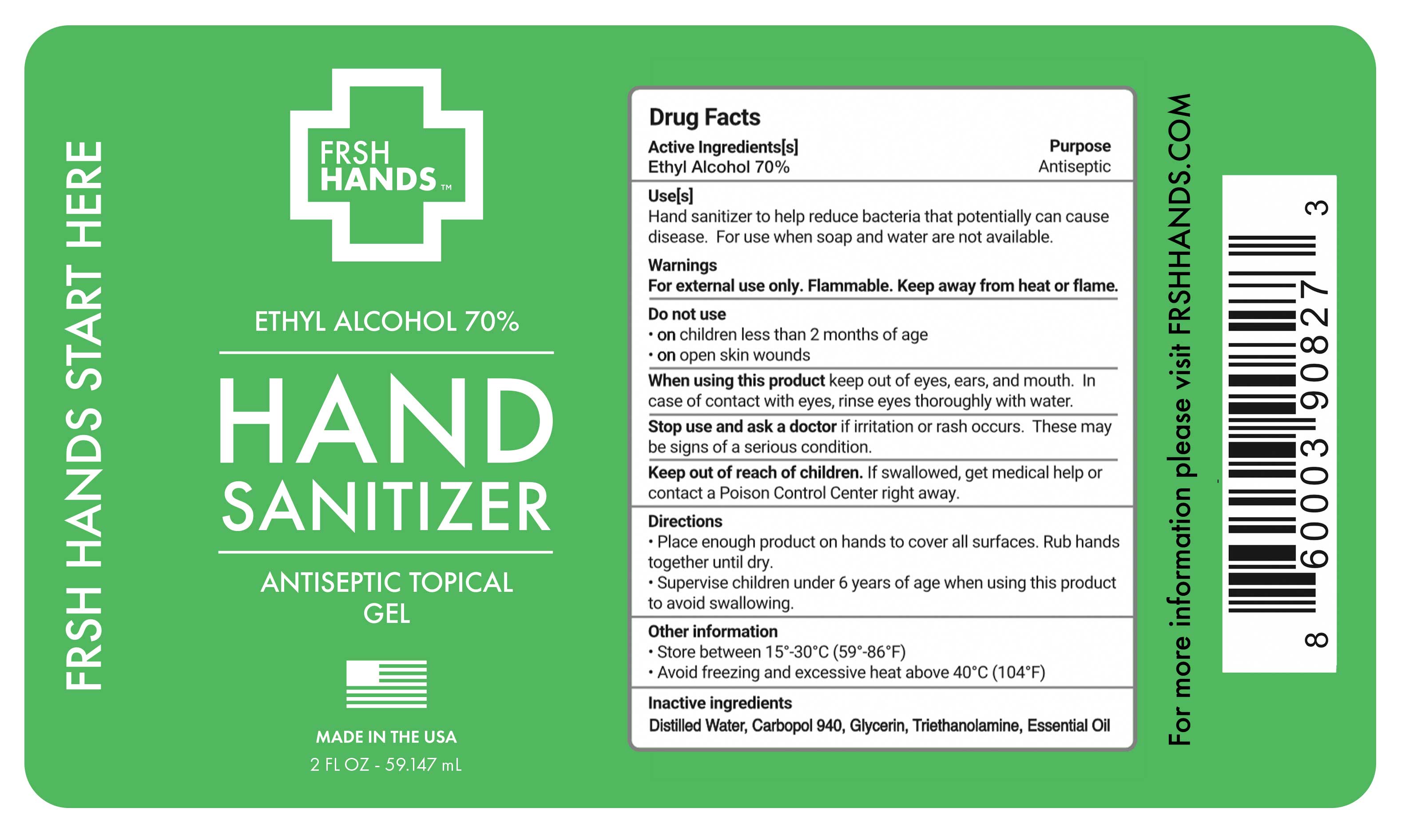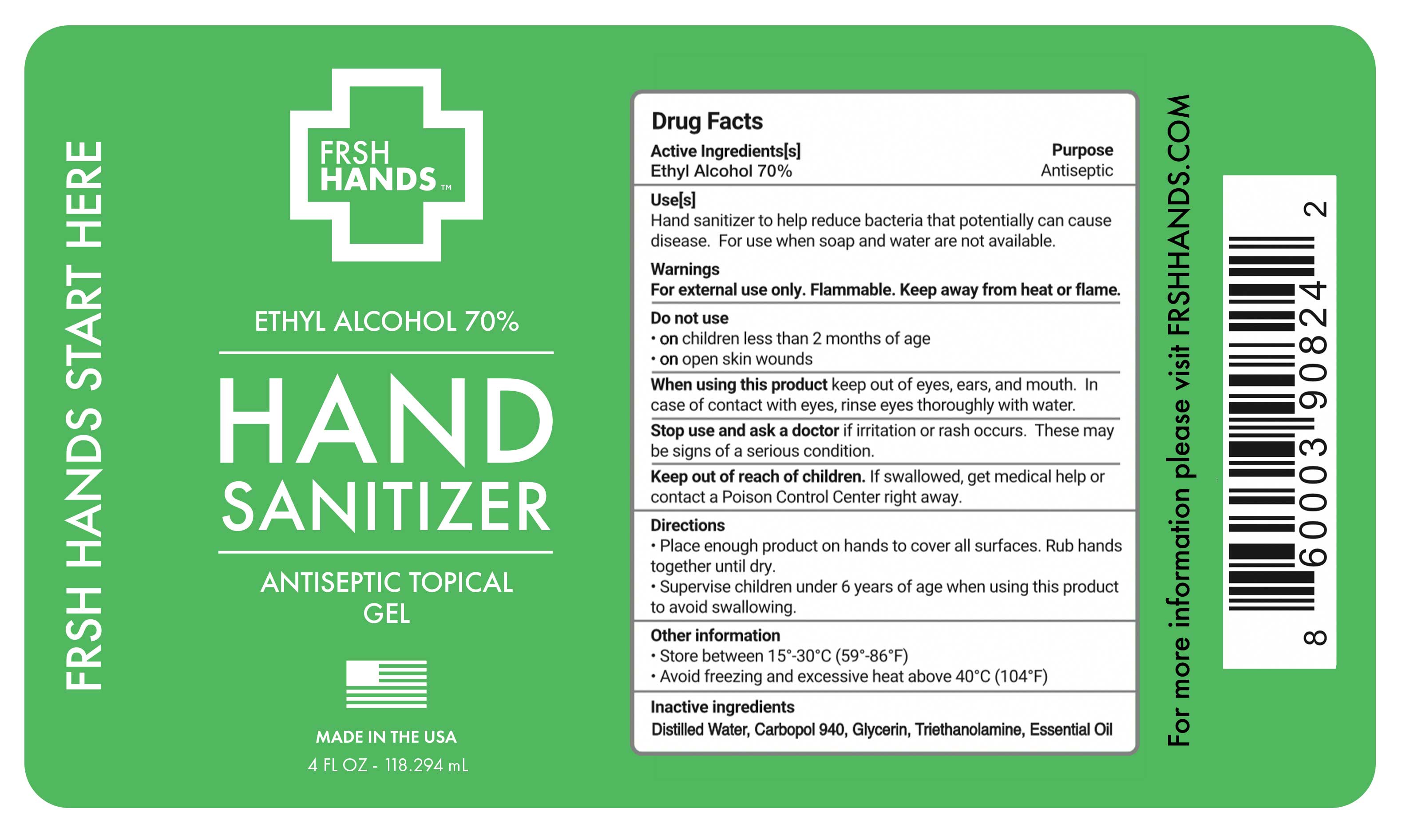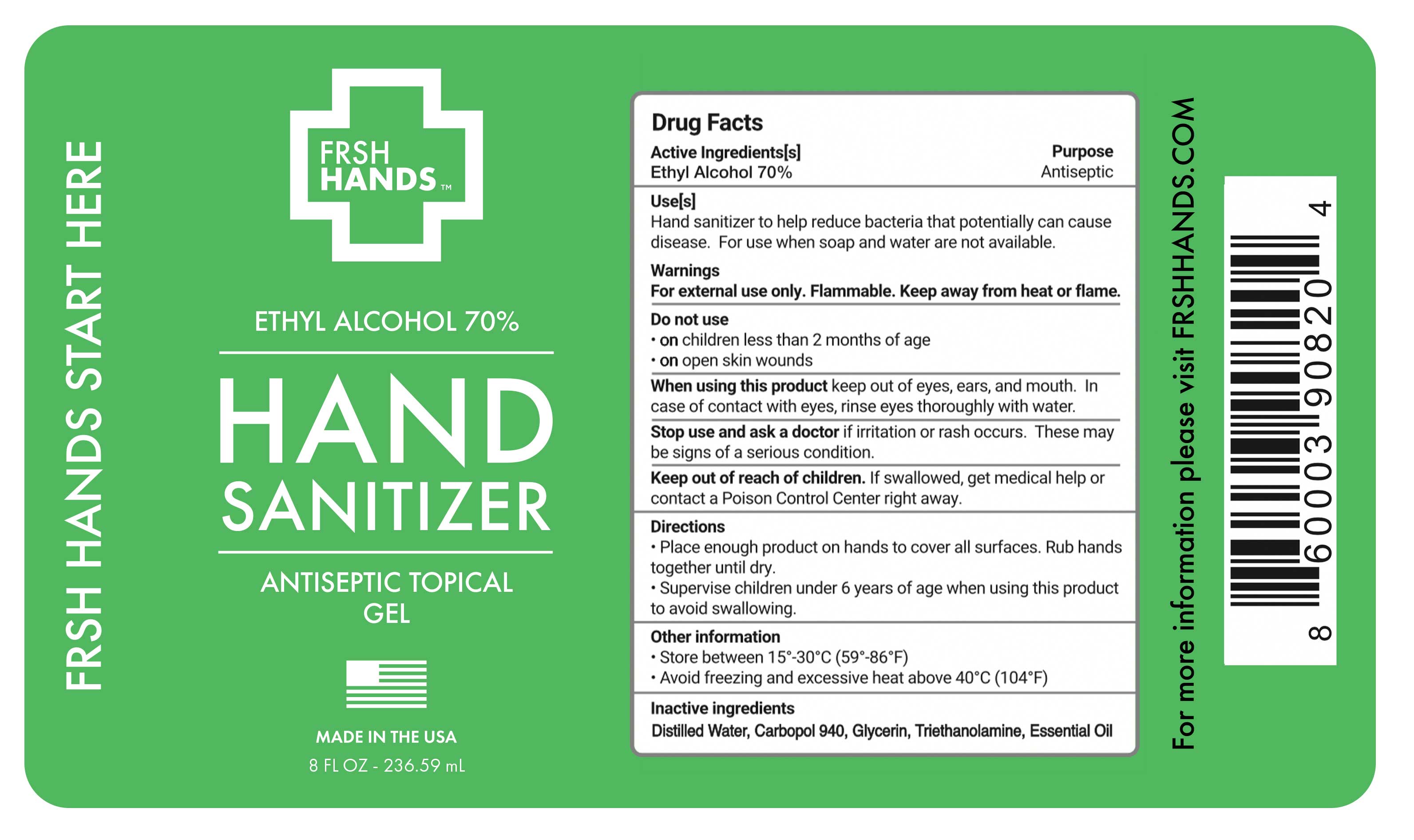 DRUG LABEL: Hand Sanitizer
NDC: 78217-002 | Form: GEL
Manufacturer: FRSH HANDS LLC
Category: otc | Type: HUMAN OTC DRUG LABEL
Date: 20200714

ACTIVE INGREDIENTS: ALCOHOL 70 mL/100 mL
INACTIVE INGREDIENTS: CARBOMER 940; TROLAMINE; GLYCERIN 1.45 mL/100 mL; HYDROGEN PEROXIDE 0.125 mL/100 mL; WATER

1. Alcohol (ethanol) (USP or Food Chemical Codex (FCC) grade) (70%, volume/volume (v/v)) in an aqueous solution denatured according to Alcohol and Tobacco Tax and Trade Bureau regulations in 27 CFR part 20.
2. Glycerin (1.45% v/v).
3. Carbopol 940.
4. Triethanolamine
5. Essential Oil
6. Sterile distilled water or boiled cold water.

Active Ingredient(s)

Ethyl Alcohol 70% v/v. Purpose: Antiseptic

Purpose

Antiseptic, Hand Sanitizer

Use

Hand Sanitizer to help reduce bacteria that potentially can cause disease. For use when soap and water are not available.

Warnings

For external use only. Flammable. Keep away from heat or flame

Do not use

- in children less than 2 months of age
- on open skin wounds

When using this product keep out of eyes, ears, and mouth. In case of contact with eyes, rinse eyes thoroughly with water.
Stop use and ask a doctor if irritation or rash occurs. These may be signs of a serious condition.
KEEP OUT OF REACH OF CHILDREN. If swallowed, get medical help or contact a Poison Control Center right away.

Stop use and ask a doctor if irritation or rash occurs. These may be signs of a serious condition.

KEEP OUT OF REACH OF CHILDREN. If swallowed, get medical help or contact a Poison Control Center right away.

Directions

- Place enough product on hands to cover all surfaces. Rub hands together until dry.
- Supervise children under 6 years of age when using this product to avoid swallowing.

Other information

- Store between 15-30C (59-86F)
- Avoid freezing and excessive heat above 40C (104F)

Inactive ingredients

Distilled Water, Carbopol 940, Glycerin, Triethanolamine, Essential Oil

Package Label - Principal Display Panel

59.147 mL NDC: 78217-002-01

118.294 mL NDC: 78217-002-02

236.59 mL NDC: 78217-002-03

473.176 mL NDC: 78217-002-04

3785 mL NDC: 78217-002-05